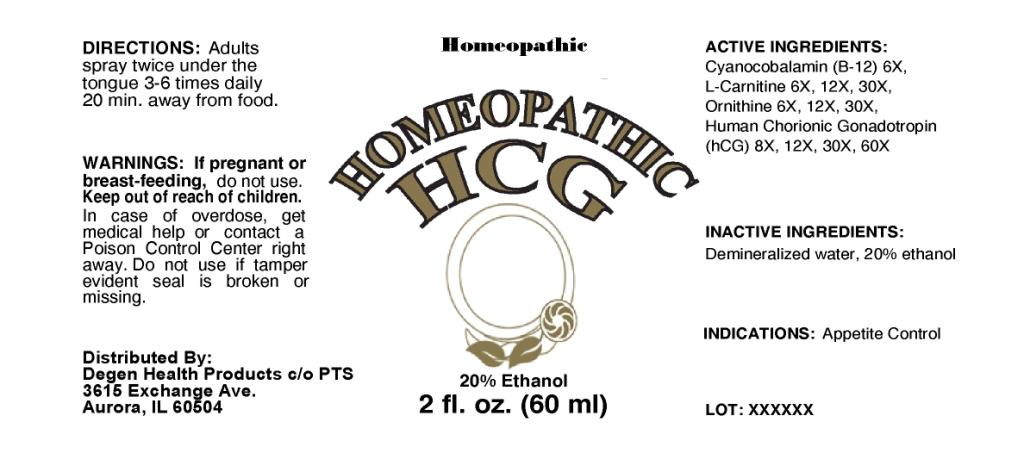 DRUG LABEL: homeopathic HCG
NDC: 57520-0161 | Form: SPRAY
Manufacturer: Apotheca Company
Category: homeopathic | Type: HUMAN OTC DRUG LABEL
Date: 20100902

ACTIVE INGREDIENTS: CYANOCOBALAMIN 6 [hp_X]/1 mL; LEVOCARNITINE 30 [hp_X]/1 mL; ORNITHINE 30 [hp_X]/1 mL; HUMAN CHORIONIC GONADOTROPIN 60 [hp_X]/1 mL
INACTIVE INGREDIENTS: WATER; ALCOHOL

ACTIVE INGREDIENT

ACTIVE INGREDIENTS: Cyanocobalamin(B-12) 6X, L-carnitine 6X, 12X, 30X, Ornithine 6X, 12X, 30X, Human chorionic gonadotropin(hCG) 8X, 12X, 30X, 60X.

PURPOSE

INDICATIONS: Appetite control.

WARNINGS

WARNINGS: If pregnant or breast-feeding, do not use.

Keep out of reach of children. In case of overdose, get medical help or contact a Poison Control Center right away.

Do not use if tamper evident seal is broken or missing.

DOSAGE AND ADMINISTRATION

DIRECTIONS: Adults spray twice under the tongue 3-6 times daily 20 min. away from food.

INACTIVE INGREDIENTS: Demineralized water, 20% Ethanol.

KEEP OUT OF REACH OF CHILDREN: In case of overdose, get medical help or contact a Poison Control Center right away.

INDICATIONS: Appetite control.

QUESTIONS

Distributed By:

Degen Health Products c/o PTS

3615 Exchange Ave.

Aurora, IL 60504

PACKAGE LABEL

Homeopathic

HOMEOPATHIC HCG

2 fl. oz. (60 ml)